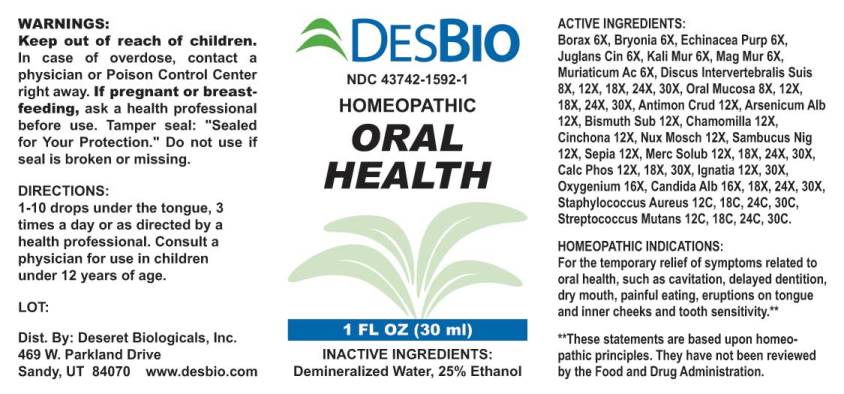 DRUG LABEL: Oral Health
NDC: 43742-1592 | Form: LIQUID
Manufacturer: Deseret Biologicals, Inc.
Category: homeopathic | Type: HUMAN OTC DRUG LABEL
Date: 20240305

ACTIVE INGREDIENTS: SODIUM BORATE 6 [hp_X]/1 mL; BRYONIA ALBA ROOT 6 [hp_X]/1 mL; ECHINACEA PURPUREA WHOLE 6 [hp_X]/1 mL; JUGLANS CINEREA BRANCH BARK/ROOT BARK 6 [hp_X]/1 mL; POTASSIUM CHLORIDE 6 [hp_X]/1 mL; MAGNESIUM CHLORIDE 6 [hp_X]/1 mL; HYDROCHLORIC ACID 6 [hp_X]/1 mL; SUS SCROFA INTERVERTEBRAL DISC 8 [hp_X]/1 mL; SUS SCROFA ORAL MUCOSA 8 [hp_X]/1 mL; ANTIMONY TRISULFIDE 12 [hp_X]/1 mL; ARSENIC TRIOXIDE 12 [hp_X]/1 mL; BISMUTH SUBNITRATE 12 [hp_X]/1 mL; MATRICARIA CHAMOMILLA WHOLE 12 [hp_X]/1 mL; CINCHONA OFFICINALIS BARK 12 [hp_X]/1 mL; NUTMEG 12 [hp_X]/1 mL; SAMBUCUS NIGRA FLOWERING TOP 12 [hp_X]/1 mL; SEPIA OFFICINALIS JUICE 12 [hp_X]/1 mL; MERCURIUS SOLUBILIS 12 [hp_X]/1 mL; TRIBASIC CALCIUM PHOSPHATE 12 [hp_X]/1 mL; STRYCHNOS IGNATII SEED 12 [hp_X]/1 mL; OXYGEN 16 [hp_X]/1 mL; CANDIDA ALBICANS 16 [hp_X]/1 mL; STAPHYLOCOCCUS AUREUS 12 [hp_C]/1 mL; STREPTOCOCCUS MUTANS 12 [hp_C]/1 mL
INACTIVE INGREDIENTS: WATER; ALCOHOL

DRUG FACTS:

ACTIVE INGREDIENTS:

Borax 6X, Bryonia (Alba) 6X, Echinacea Purpurea 6X, Juglans Cinerea 6X, Kali Muriaticum 6X, Magnesia Muriatica 6X, Muriaticum Acidum 6X, Discus Intervertebralis Suis 8X, 12X, 18X, 24X, 30X, Oral Mucosa (Suis) 8X, 12X, 18X, 24X, 30X, Antimonium Crudum 12X, Arsenicum Album 12X, Bismuthum Subnitricum 12X, Chamomilla 12X, Cinchona Officinalis 12X, Nux Moschata 12X, Sambucus Nigra 12X, Sepia 12X, Mercurius Solubilis 12X, 18X, 24X, 30X, Calcarea Phosphorica 12X, 18X, 30X, Ignatia Amara 12X, 30X, Oxygenium 16X, Candida Albicans 16X, 18X, 24X, 30X, Staphylococcus Aureus 12C, 18C, 24C, 30C, Streptococcus Mutans 12C, 18C, 24C, 30C.

HOMEOPATHIC INDICATIONS:

For the temporary relief of symptoms related to oral health, such as cavitation, delayed dentition, dry mouth, painful eating, eruptions on tongue and inner cheeks and tooth sensitivity.**

**These statements are based upon homeopathic principles. They have not been reviewed by the Food and Drug Administration.

WARNINGS:

Keep out of reach of children. In case of overdose, Contact a physician or Poison Control Center right away.

If pregnant or breast-feeding, ask a health professional before use.

Tamper seal: "Sealed for Your Protection." Do not use if seal is broken or missing.

Keep out of reach of children. In case of overdose, contact a physician or Poison Control Center right away.

DIRECTIONS:

1-10 drops under the tongue, 3 times a day or as directed by a health professional. Consult a physician for use in children under 12 years of age.

HOMEOPATHIC INDICATIONS:

For the temporary relief of symptoms related to oral health, such as cavitation, delayed dentition, dry mouth, painful eating, eruptions on tongue and inner cheeks and tooth sensitivity.**

**These statements are based upon homeopathic principles. They have not been reviewed by the Food and Drug Administration.

INACTIVE INGREDIENTS:

Demineralized Water, 25% Ethanol.

QUESTIONS:

Dist. By: Deseret Biologicals, Inc.

469 W. Parkland Drive

Sandy, UT 84070 www.desbio.com

PACKAGE LABEL DISPLAY:

DESBIO
NDC 43742-1592-1
HOMEOPATHIC
ORAL
HEALTH
1 FL OZ (30 ml)